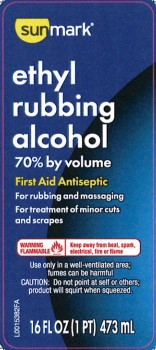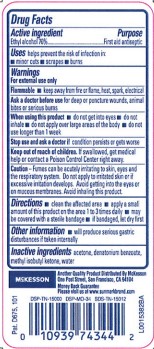 DRUG LABEL: Ethyl Rubbing Alcohol
NDC: 70677-0056 | Form: LIQUID
Manufacturer: STRATEGIC SOURCING SERVICES LLC
Category: otc | Type: HUMAN OTC DRUG LABEL
Date: 20260217

ACTIVE INGREDIENTS: ALCOHOL 70 mL/100 mL
INACTIVE INGREDIENTS: ACETONE; DENATONIUM BENZOATE; METHYL ISOBUTYL KETONE; WATER

Sunmark 876.002/876AL
Ethyl Rubbing Alcohol

Active Ingredient

Ethyl alcohol 70%

Purpose

First aid antiseptic

Use

first aid to help prevent the risk of infection in:

- minor cuts
- scrapes
- burns

Warnings

For external use only.

Flammable.

- Keep away from fire or flame, heat, spark, electrical

Ask a doctor before use

for deep or puncture wounds, animal bites or serious burns

When using this product

- do not get into eyes
- do not inhale
- do not apply over large areas of the body
- do not use longer than 1 week

Stop use and ask a doctor if

condition persists or gets worse

Keep out of reach of children.

If swallowed, get medical help or contact a Poison Control Center right away.

Caution

Fumes can be acutely irritating to skin, eyes and the respiratory system. Do not apply to irritated skin or if excessive irritation develops. Avoid getting into the eyes or on mucous membranes. Avoid inhaling this product.

Directions

- clean the affected area
- apply a small amount of this product on the affected area 1 to 3 times daily
- may be covered with a sterile bandage
- if bandaged, let dry first

Other information

will produce serious gastric disturbances if taken internally

Inactive ingredient

acetone, denatonium benzoate, methyl isobutyl ketone, water

ADVERSE REACTION

McKesson

Another Quality Product Distributed by McKesson

One Post Street, San Francisco, CA 94104

Money Back Guarantee

Please visit us at www.sunmarkbrand.com

DSP-TN-15000

DSP-MO-34

SDS-TN-15012

Pat. D675,101

principal display panel

Sunmark®

Ethyl rubbing alcohol 70% by volume

First Aid Antseptic

For rubbing and massaging

For treatment of minor cuts and scrapes

WARNING FLAMMABLE - Keep away from heat, spark, electrical, fire or flame

Use only in well-ventilated area; fumes can be harmful

CAUTION: Do not point at self or others; product will squirt when squeezed.

16 FL OZ (1 PT) 473 mL